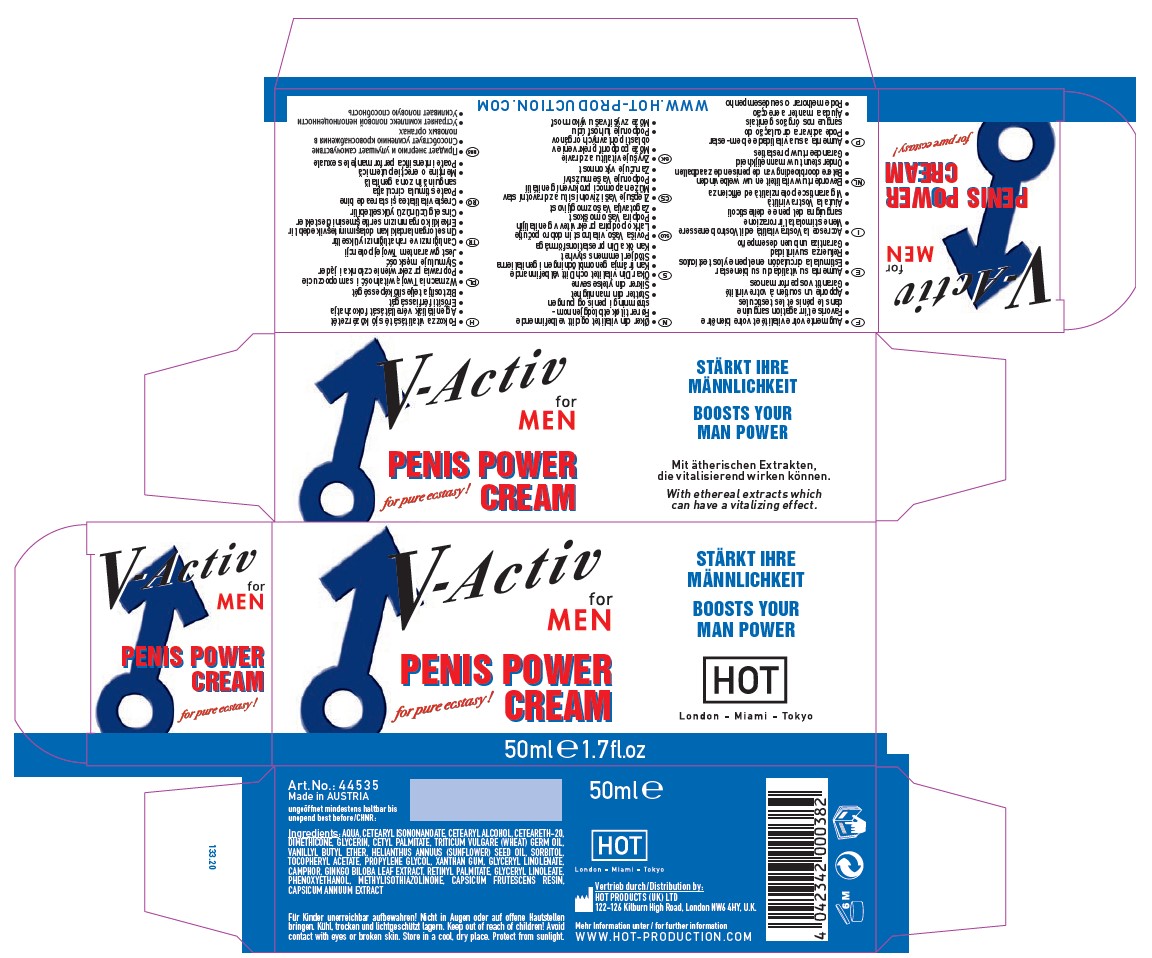 DRUG LABEL: V-ACTIV FOR MEN
NDC: 71326-203 | Form: CREAM
Manufacturer: HOT PRODUCTIONS AND VERTRIEBS GMBH
Category: homeopathic | Type: HUMAN OTC DRUG LABEL
Date: 20231005

ACTIVE INGREDIENTS: CAPSICUM ANNUUM WHOLE 0.1 g/100 mL; CAPSICUM FRUTESCENS WHOLE 0.1 g/100 mL; GINKGO 1 g/100 mL
INACTIVE INGREDIENTS: XANTHAN GUM; GLYCERYL LINOLENATE; PROPYLENE GLYCOL; PHENOXYETHANOL; METHYLISOTHIAZOLINONE; .ALPHA.-TOCOPHEROL ACETATE; CETOSTEARYL ALCOHOL; VANILLYL BUTYL ETHER; WHEAT GERM OIL; CETEARYL ISONONANOATE; GLYCERIN; SUNFLOWER OIL; POLYOXYL 20 CETOSTEARYL ETHER; DIMETHICONE; CETYL PALMITATE; WATER; SORBITOL

HOT PRODUCTS - V-ACTIV FOR MEN CREAM (71326-203)

ACTIVE INGREDIENTS

GINKGO BILOBA 1X HPUS

CAPSISUM FRUTESCENS 0.1X HPUS

CAPSICUM ANNUUM EXTRACT 0.1X HPUS

PURPOSE

Topical Anesthetic

USE

V-Activ Penis Power Cream can have an immediate and highly pleasurable effect boosting the blood circulation to the penis. To add a highly erotic note to foreplay have your partner massage in cream. The sexual potency of the man is strengthened and the love
act is fueled driven by pure passion. For a spontaneous pleasurable effect, apply cream immediately before the sexual act.

WARNINGS

Avoid contact with the eyes or broken skin.

Keep out of reach of children.

DIRECTIONS

Apply about a fingertip full of V-Activ Penis Power Cream to the penis and scrotum and massage in gently until the cream has been absorbed. Wait about 5 minutes until the creme has soaked in thoroughly before using a condom.

OTHER INFORMATION

- Store in a cool, dry place. Protect from sunlight.

INACTIVE INGREDIENTS

AQUA, CETEARYL ISONONANOATE, CETEARYL ALCOHOL, CETEARETH-20, DIMETHICONE, GLYCERIN, CETYL PALMITATE, TRITICUM VULGARE (WHEAT) GERM OIL, VANILLYL BUTYL ETHER, HELIANTHUS ANNUUS (SUNFLOWER) SEED OIL, SORBITOL, TOCOPHERYL ACETATE, PROPYLENE GLYCOL, XANTHAN GUM, GLYCERYL LINOLENATE, CAMPHOR, RETINYL PALMITATE, GLYCERYL LINOLEATE, PHENOXYETHANOL, METHYLISOTHIAZOLINONE,